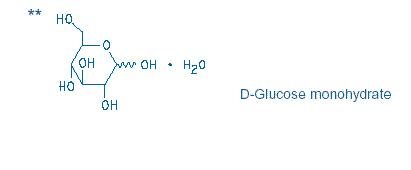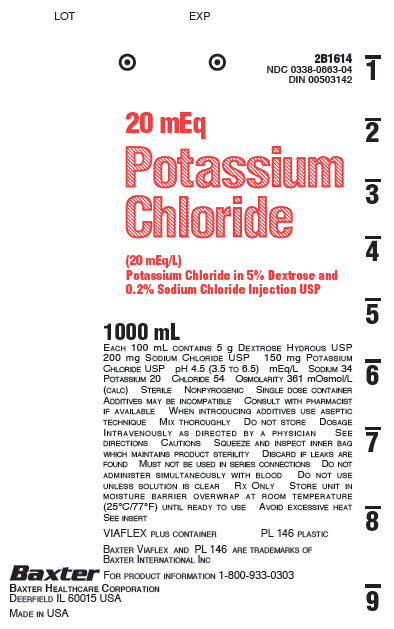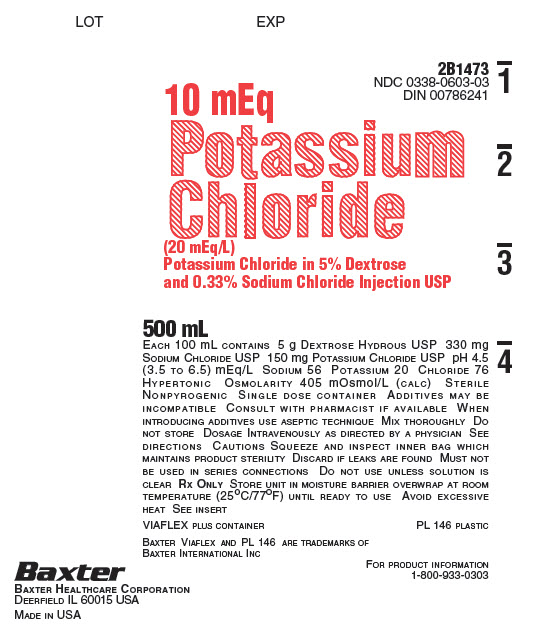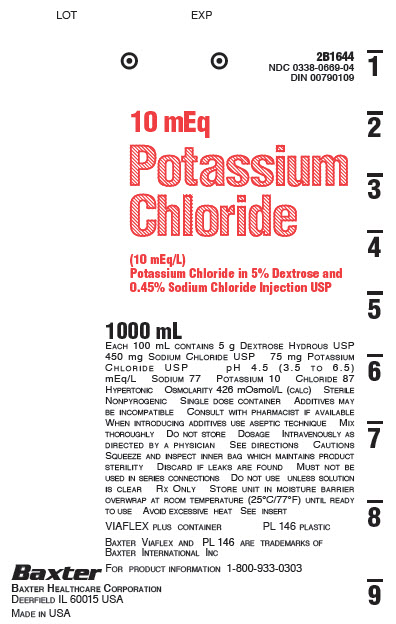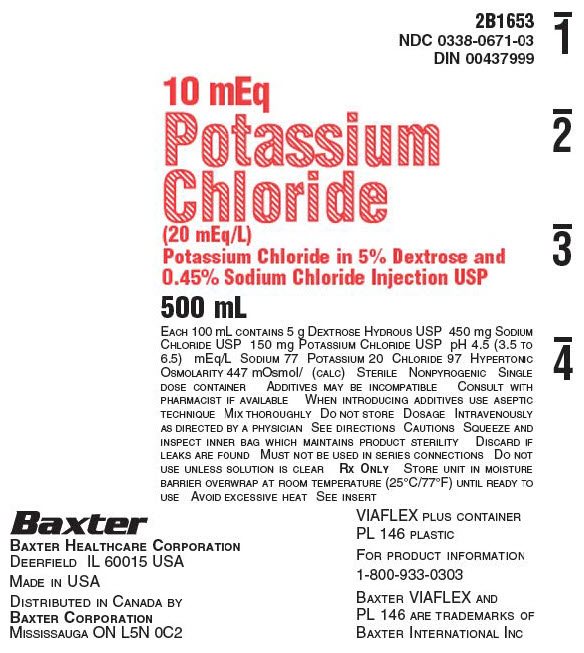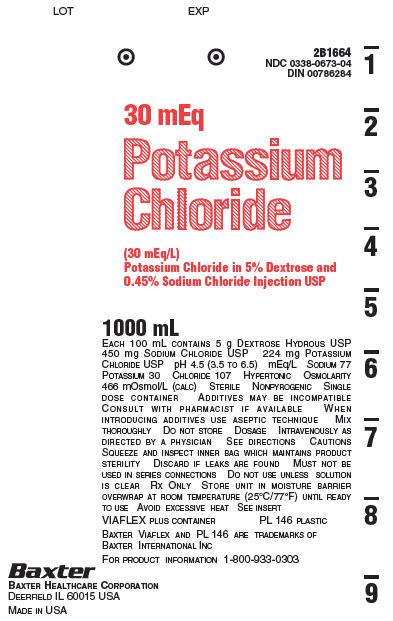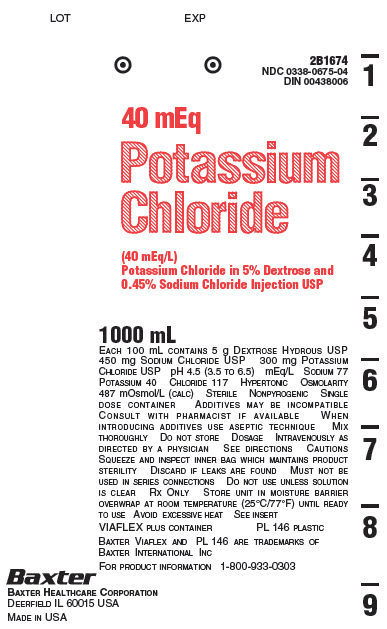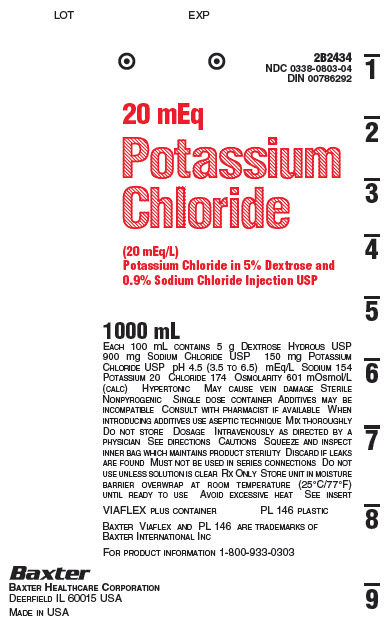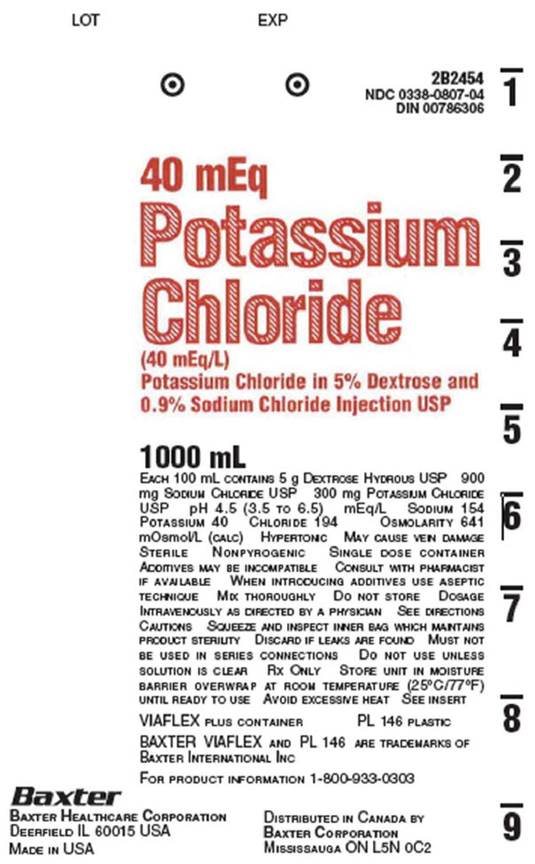 DRUG LABEL: Potassium Chloride in Dextrose and Sodium Chloride
NDC: 0338-0663 | Form: INJECTION, SOLUTION
Manufacturer: Baxter Healthcare Company
Category: prescription | Type: HUMAN PRESCRIPTION DRUG LABEL
Date: 20190221

ACTIVE INGREDIENTS: POTASSIUM CHLORIDE 150 mg/100 mL; DEXTROSE MONOHYDRATE 5 g/100 mL; SODIUM CHLORIDE 200 mg/100 mL
INACTIVE INGREDIENTS: WATER

HIGHLIGHTS OF PRESCRIBING INFORMATION

These highlights do not include all the information needed to use POTASSIUM CHLORIDE IN DEXTROSE AND SODIUM CHLORIDE INJECTION safely and effectively. See full prescribing information for POTASSIUM CHLORIDE IN DEXTROSE AND SODIUM CHLORIDE INJECTION.
POTASSIUM CHLORIDE IN DEXTROSE AND SODIUM CHLORIDE injection, for intravenous use
Initial U.S. Approval: 1979

RECENT MAJOR CHANGES

Contraindications (4) 02/2019
Warnings and Precautions (5.1, 5.2, 5.3, 5.4, 5.5, 5.6, 5.7) 02/2019

1 INDICATIONS AND USAGE

Potassium Chloride in Dextrose and Sodium Chloride Injection is indicated as a source of water, electrolytes and calories. (1)

2 DOSAGE AND ADMINISTRATION

- Only for intravenous infusion. (2.1, 5.2)
- See full prescribing information for information on preparation, administration, dosing considerations and instructions for use. (2.1, 2.2, 2.3)

3 DOSAGE FORMS AND STRENGTHS

Potassium Chloride in Dextrose and Sodium Chloride Injection is available in multiple strengths. See full prescribing information for detailed description of each formulation. (3)

4 CONTRAINDICATIONS

- Known hypersensitivity to potassium chloride, dextrose, or sodium chloride (4, 5.1)
- Clinically significant hyperkalemia (4, 5.2)
- Clinically significant hyperglycemia (4, 5.3)

5 WARNINGS AND PRECAUTIONS

- Hypersensitivity Reactions: monitor for signs and symptoms and discontinue infusion if reactions occur. (5.1)
- Hyperkalemia: May result in cardiac arrhythmias. Avoid use in patients with, or at risk for, hyperkalemia. If use cannot be avoided, use a product with a low amount of potassium chloride, infuse slowly and monitor serum potassium concentrations and ECGs. (5.2)
- Hyperglycemia or Hyperosmolar Hyperglycemic State: Monitor blood glucose and administer insulin as needed. (5.3, 8.4)
- Hyponatremia, Hypernatremia and Hyperchloremia: Avoid in patients with or at risk for hypo-/hypernatremia. If use cannot be avoided, monitor serum sodium concentrations. (5.4, 5.5, 8.4)
- Fluid Overload: Avoid in patients with or at risk for fluid and/or solute overloading. If use cannot be avoided, monitor daily fluid balance and electrolyte, concentrations and acid-base balance, as needed and especially during prolonged use. (5.6)
- Refeeding Syndrome: Monitor severely undernourished patients and slowly increase nutrient intake. (5.7)

6 ADVERSE REACTIONS

Adverse reactions include electrolyte imbalances, hyperglycemia, and hypervolemia and injection site reactions. (6)

To report SUSPECTED ADVERSE REACTIONS, contact Baxter Healthcare at 1-866-888-2472 or FDA at 1-800-FDA-1088 or www.fda.gov/medwatch.

7 DRUG INTERACTIONS

- Other Products that Cause Hyperkalemia: Avoid use in patients receiving such products. If use cannot be avoided, monitor serum potassium concentrations. (7.1)
- Lithium: Decreased lithium concentrations with concomitant use; monitor serum lithium concentrations. (7.2)
- Other Products that Affect Glycemic Control, Vasopressin or Fluid and/or Electrolyte Balance: Monitor blood glucose concentrations, fluid balance serum electrolyte concentrations and acid-base balance. (7.3)

FULL PRESCRIBING INFORMATION

1 INDICATIONS AND USAGE

Potassium Chloride in Dextrose and Sodium Chloride Injection is indicated as a source of water, electrolytes and calories.

2 DOSAGE AND ADMINISTRATION

2.1 Important Administration Instructions

- Potassium Chloride in Dextrose and Sodium Chloride Injection is only for intravenous infusion [see Warnings and Precautions (5.2)].
- The osmolarity of Potassium Chloride in Dextrose and Sodium Chloride Injection, ranges from 361 to 641 mOsmol/L (calc). Peripheral administration is generally acceptable; however; consider central vein administration if there is peripheral vein irritation, phlebitis, and/or associated pain especially with higher potassium concentrations.
- Do not administer Potassium Chloride in Dextrose and Sodium Chloride Injection simultaneously with blood products through the same administration set because of the possibility of pseudoagglutination or hemolysis.
- To prevent air embolism, use a non-vented infusion set or close the vent on a vented set, avoid multiple connections, do not connect flexible containers in series, fully evacuate residual gas in the container prior to administration, do not pressurize the flexible container to increase flow rates, and if administration is controlled by a pumping device, turn off pump before the container runs dry.
- Prior to infusion, visually inspect the solution for particulate matter. The solution should be clear and there should be no precipitates. Do not administer unless solution is clear and container is undamaged.
- Use of a final filter is recommended during administration of parenteral solutions, where possible.

2.2 Recommended Dosage

The choice of the specific potassium chloride, sodium chloride, and dextrose concentrations, rate and volume depends on the age, weight, clinical and metabolic conditions of the patient and concomitant therapy. Electrolyte supplementation may be indicated according to the clinical needs of the patient.

The administration rate should be governed, especially for premature infants with low birth weight, during the first few days of therapy, by the patient’s tolerance to dextrose. Increase the infusion rate gradually as indicated by frequent monitoring of blood glucose concentrations [see Warnings and Precautions (5.1), Use in Specific Populations (8.4)].

2.3 Instructions for Use

To Open

- Do not remove container from overwrap until ready to use.
- Tear overwrap down side at slit and remove solution container.
- Visually inspect the container. Some opacity of the plastic due to moisture absorption during the sterilization process may be observed. This is normal and does not affect the solution quality or safety. The opacity will diminish gradually.
  Evaluate the following:
  - If the outlet port protector is damaged, detached, or not present, discard container.
  - Check to ensure the solution is clear and there are no precipitates. Discard if there is a color change and/or the appearance of precipitates, insoluble complexes or crystals.
  - Check for minute leaks by squeezing inner bag firmly. If leaks are found, discard container.

Preparation for Administration

1. Suspend container from eyelet support.
2. Remove protector from outlet port at bottom of container.
3. Attach administration set. Refer to complete directions accompanying set.

To Add Medication

- Additives may be incompatible. Complete information is not available. Do not use additives known or determined to be incompatible.
- Consult with pharmacist, if available. If, in the informed judgment of the healthcare provider, it is deemed advisable to introduce additives, use aseptic technique.
- When introducing additives, consult the instructions for use of the medication to be added and other relevant literature.
- Before adding a substance or medication, verify that it is soluble and/or stable in Potassium Chloride in Dextrose and Sodium Chloride Injection and that the pH range of Potassium Chloride in Dextrose and Sodium Chloride Injection is appropriate.

To Add Medication Before Solution Administration

1. Prepare medication site.
2. Using syringe with 19 to 22 gauge needle, puncture resealable medication port and inject.
3. Mix solution and medication thoroughly. For high density medication such as potassium chloride, squeeze ports while ports are upright and mix thoroughly.
4. After addition, check to ensure the solution is clear and there are no precipitates. Discard if there is a color change and/or the appearance of precipitates, insoluble complexes or crystals.

To Add Medication During Solution Administration

1. Close clamp on the set.
2. Prepare medication site.
3. Using syringe with 19 to 22 gauge needle, puncture resealable medication port and inject.
4. Remove container from IV pole and/or turn to an upright position.
5. Evacuate both ports by squeezing them while container is in the upright position.
6. Mix solution and medication thoroughly.
7. After addition, check to ensure the solution is clear and there are no precipitates. Discard if there is a color change and/or the appearance of precipitates, insoluble complexes or crystals, do not use.

Storage

- Use promptly; do not store solutions containing additives.
- Single-dose container.
- Discard any unused portion.

3 DOSAGE FORMS AND STRENGTHS

Potassium Chloride in Dextrose and Sodium Chloride Injection, USP are clear solutions in 500 mL and 1000 mL single-dose, flexible containers:

500 mL flexible container

- 10 mEq/500 mL Potassium Chloride, 5% Dextrose and 0.2% Sodium Chloride
- 10 mEq/500 mL Potassium Chloride, 5% Dextrose and 0.33% Sodium Chloride
- 10 mEq/500 mL Potassium Chloride, 5% Dextrose and 0.45% Sodium Chloride

1000 mL flexible container

- 20 mEq/L Potassium Chloride, 5% Dextrose and 0.2% Sodium Chloride
- 10 mEq/L Potassium Chloride, 5% Dextrose and 0.45% Sodium Chloride
- 20 mEq/L Potassium Chloride, 5% Dextrose and 0.45% Sodium Chloride
- 30 mEq/L Potassium Chloride, 5% Dextrose and 0.45% Sodium Chloride
- 40 mEq/L Potassium Chloride, 5% Dextrose and 0.45% Sodium Chloride
- 20 mEq/L Potassium Chloride, 5% Dextrose and 0.9% Sodium Chloride
- 40 mEq/L Potassium Chloride, 5% Dextrose and 0.9% Sodium Chloride

4 CONTRAINDICATIONS

Potassium Chloride in Dextrose and Sodium Chloride Injection is contraindicated in patients with:

- known hypersensitivity to potassium chloride, dextrose and/or sodium chloride [see Warnings and Precautions 5.1)]
- clinically significant hyperkalemia [see Warnings and Precautions (5.2)]
- clinically significant hyperglycemia [see Warnings and Precautions (5.3)]

5 WARNINGS AND PRECAUTIONS

5.1 Hypersensitivity Reactions

Hypersensitivity and infusion reactions, including anaphylaxis, have been reported with Potassium Chloride in Dextrose and Sodium Chloride Injection [see Adverse Reactions (6)]. Stop the infusion immediately if signs or symptoms of a hypersensitivity or infusion reaction develops [see Contraindications (4)]. Appropriate therapeutic countermeasures must be instituted as clinically indicated.

5.2 Hyperkalemia

Potassium-containing solutions, including Potassium Chloride in Dextrose and Sodium Chloride Injection may increase the risk of hyperkalemia. Hyperkalemia can be asymptomatic and manifest only by increased serum potassium concentrations and/or characteristic electrocardiographic (ECG) changes. Cardiac arrhythmias, some fatal, can develop at any time during hyperkalemia.

To avoid life threatening hyperkalemia, do not administer Potassium Chloride in Dextrose and Sodium Chloride Injection as an intravenous push (i.e., intravenous injection manually with a syringe connected to the intravenous access, without quantitative infusion device [see Dosage and Administration (2.1)].

Patients at increased risk of developing hyperkalemia and cardiac arrhythmias include those:

- with severe renal impairment, acute dehydration, extensive tissue injury or burns, and certain cardiac disorders such as congestive heart failure or AV block (especially if they receive digoxin).
- with hyperosmolality, acidosis, or undergoing correction of alkalosis (conditions associated with a shift of potassium from intracellular to extracellular space).
- treated concurrently or recently with agents or products that can cause or increase the risk of hyperkalemia [see Drug Interactions (7.1)].

Avoid use of Potassium Chloride in Dextrose and Sodium Chloride Injection in patients with, or at risk for, hyperkalemia. If use cannot be avoided, use a product with a low amount of potassium chloride, infuse slowly and monitor serum potassium concentrations and ECGs.

5.3 Hyperglycemia and Hyperosmolar Hyperglycemic State

The use of dextrose infusions in patients with impaired glucose tolerance may worsen hyperglycemia. Administration of dextrose at a rate exceeding the patient’s utilization rate may lead to hyperglycemia, coma, and death.

Hyperglycemia is associated with an increase in serum osmolality, resulting in osmotic diuresis, dehydration and electrolyte losses [see Warnings and Precautions (5.6)]. Patients with underlying central nervous system disease and renal impairment who receive dextrose infusions, may be at greater risk of developing hyperosmolar hyperglycemic state.

Monitor blood glucose concentrations and treat hyperglycemia to maintain concentrations within normal limits while administering Potassium Chloride in Dextrose and Sodium Chloride Injection. Insulin may be administered or adjusted to maintain optimal blood glucose concentrations.

5.4 Hyponatremia

Potassium Chloride in Dextrose and Sodium Chloride Injection is a hypertonic solution [see Description, Table 1 (11)]. In the body, however, glucose containing fluids can become extremely physiologically hypotonic due to rapid glucose metabolization. Monitoring of serum sodium is particularly important for hypotonic fluids.

Depending on the tonicity of the solution, the volume and rate of infusion, and depending on a patient’s underlying clinical condition and capability to metabolize glucose, intravenous administration of glucose can cause electrolyte disturbances, most importantly hypo- or hyperosmotic hyponatremia.

The risk for hyponatremia is increased, in pediatric patients, elderly patients, postoperative patients, those with psychogenic polydipsia and in patients treated with medications that increase the risk of hyponatremia (such as certain diuretic, antiepileptic and psychotropic medications). Close clinical monitoring may be warranted.

Acute hyponatremia can lead to acute hyponatremic encephalopathy characterized by headache, nausea, seizures, lethargy and vomiting. Patients with brain edema are at particular risk of severe, irreversible and life-threatening brain injury. Patients at increased risk for developing complications of hyponatremia, such as hyponatremic encephalopathy include pediatric patients; women, in particular, premenopausal women; patients with hypoxemia; and in patients with underlying central nervous system disease [see Use in Specific Populations (8.4, 8.5)].

Avoid solutions with less than 0.9% Sodium Chloride in patients with or at risk for hyponatremia. If use cannot be avoided, monitor serum sodium concentrations.

Rapid correction of hyponatremia is potentially dangerous with risk of serious neurologic complications such as osmotic demyelination syndrome with risk of seizures and cerebral edema. To avoid complications, monitor serum sodium and chloride concentrations, fluid status, acid-base balance, and signs of neurologic complications.

High volume infusion must be used with close monitoring in patients with cardiac or pulmonary failure, and in patients with non-osmotic vasopressin release (including SIADH), due to the risk of hospital-acquired hyponatremia.

5.5 Hypernatremia and Hyperchloremia

Electrolyte imbalances such as hypernatremia and hyperchloremia, leading to metabolic acidosis may occur with solutions containing 0.9% Sodium Chloride.

Conditions that may increase the risk of hypernatremia, fluid overload and edema (central and peripheral), include patients with pre-eclampsia, primary hyperaldosteronism and secondary hyperaldosteronism associated with, for example, hypertension, congestive heart failure, severe renal insufficiency, liver disease (including cirrhosis), and renal disease (including renal artery stenosis, nephrosclerosis).

Medications such as corticosteroids or corticotropin, may increase the risk of sodium and fluid retention.

Avoid in patients with or at risk for hypernatremia. If use cannot be avoided, monitor serum sodium concentrations.

Rapid correction of hypernatremia is potentially dangerous with risk of serious neurologic complications. Excessively rapid correction of hypernatremia is also associated with a risk for serious neurologic complications such as osmotic demyelination syndrome (ODS) with risk of seizures and cerebral edema.

5.6 Fluid Overload

Depending on the volume and rate of infusion, the patient’s underlying clinical condition and capability to metabolize dextrose, intravenous administration of Potassium Chloride in Dextrose and Sodium Chloride Injection can cause fluid and/or solute overloading resulting in dilution of serum electrolyte concentrations, overhydration, congested states or pulmonary edema.

Avoid Potassium Chloride in Dextrose and Sodium Chloride Injection in patients with or at risk for fluid and/or solute overloading. If use cannot be avoided, monitor fluid balance, electrolyte concentrations, and acid-base balance as needed and especially during prolonged use.

5.7 Refeeding Syndrome

Refeeding severely undernourished patients may result in the refeeding syndrome that is characterized by the shift of potassium, phosphorus, and magnesium intracellularly as the patient becomes anabolic. Thiamine deficiency and fluid retention may also develop. To prevent these complications, monitor severely undernourished patients and slowly increasing nutrient intake.

6 ADVERSE REACTIONS

The following adverse reactions associated with the use of Potassium Chloride in Dextrose and Sodium Chloride Injection were identified in postmarketing reports. Because these reactions were reported voluntarily from a population of uncertain size, it is not always possible to reliably estimate their frequency or establish a causal relationship to drug exposure.

The following clinically significant adverse reactions are described elsewhere in the labeling:

- Hypersensitivity Reactions: anaphylaxis, rash and pruritus [see Warnings and Precautions (5.1)].
- Metabolism and Nutrition Disorders: hyperkalemia [see Warnings and Precautions (5.2)], hyperglycemia and hyperosmolar hyperglycemic state [see Warnings and Precautions (5.3)], hyponatremia and hyponatremic encephalopathy [see Warnings and Precautions (5.4)], fluid overload [see Warnings and Precautions (5.6)] and refeeding syndrome [see Warnings and Precautions (5.2)]. Hypernatremia and hyperchloremia acidosis [see Warnings and Precautions (5.5)] have been observed in solutions containing 0.9% sodium chloride.
- Cardiac Disorder: cardiac arrest as a manifestation of rapid intravenous administration and/or of hyperkalemia [see Warnings and Precautions (5.2)].
- Infusion Site Reactions: injection site vesicles, extravasation, venous thrombosis or phlebitis, infusion site pain.

7 DRUG INTERACTIONS

7.1 Other Products that Cause Hyperkalemia

Administration of Potassium Chloride in Dextrose and Sodium Chloride Injection in patients treated concurrently or recently with other products that can cause hyperkalemia or increase the risk of hyperkalemia (e.g., potassium-sparing diuretics, angiotensin-converting enzyme inhibitors, angiotensin receptor blockers) increases the risk of severe and potentially fatal hyperkalemia, in particular in the presence of other risk factors for hyperkalemia [see Warnings and Precautions (5.2)]. Avoid use of Potassium Chloride in Dextrose and Sodium Chloride Injection in patients receiving such products. If use cannot be avoided, monitor serum potassium concentrations.

7.2 Lithium

Renal sodium and lithium clearance may be increased during administration of Potassium Chloride in Dextrose and Sodium Chloride Injection resulting in decreased serum lithium concentrations. Monitor serum lithium concentrations during concomitant use.

7.3 Other Products that Affect Glycemic Control, Vasopressin or Fluid and/or Electrolyte Balance

Potassium Chloride in Dextrose and Sodium Chloride Injection can affect glycemic control, vasopressin and fluid and/or electrolyte balance [see Warnings and Precautions (5.3, 5.4, 5.5, 5.6)]. Monitor blood glucose concentrations, fluid balance, serum electrolyte concentrations and acid-base balance when using Potassium Chloride in Dextrose and Sodium Chloride Injection in patients treated with other substances that affect glycemic control, vasopressin or fluid and/or electrolyte balance.

8 USE IN SPECIFIC POPULATIONS

8.1 Pregnancy

Risk Summary

Appropriate administration of Potassium Chloride in Dextrose Sodium Chloride Injection during pregnancy is not expected to cause adverse developmental outcomes, including congenital malformations. Animal reproduction studies have not been conducted with Potassium Chloride in Dextrose Sodium Chloride Injection.

The estimated background risk of major birth defects and miscarriage for the indicated population is unknown. All pregnancies have a background risk of birth defect, loss, or other adverse outcomes. In the U.S. general population, the estimated background risk of major birth defects and miscarriage in clinically recognized pregnancies is 2 to 4% and 15 to 20%, respectively.

8.2 Lactation

Risk Summary

Sodium and potassium are present in human breast milk. There are no data on the effects of Potassium Chloride in Sodium Chloride and Glucose on a breastfed infant or the effects on milk production.

The developmental and health benefits of breastfeeding should be considered along with the mother’s clinical need for Potassium Chloride in Dextrose and Sodium Chloride Injection and any potential adverse effects on the breastfed infant from Potassium Chloride in Dextrose and Sodium Chloride Injection or from the underlying maternal condition.

8.4 Pediatric Use

The safety profile of Potassium Chloride in Dextrose and Sodium Chloride Injection in pediatric patients is similar to adults.

Neonates, especially premature infants with low birth weight, are at increased risk of developing hypo- or hyperglycemia and therefore need close monitoring during treatment with intravenous glucose solutions to ensure adequate glycemic control in order to avoid potential long term adverse effects.

Closely monitor plasma electrolyte concentrations in pediatric patients who may have impaired ability to regulate fluids and electrolytes. In very low birth weight infants, excessive or rapid administration of Potassium Chloride in Dextrose and Sodium Chloride Injection may result in increased serum osmolality and risk of intracerebral hemorrhage.

Children (including neonates and older children) are at increased risk of developing hyponatremia as well as for developing hyponatremic encephalopathy.

8.5 Geriatric Use

Clinical studies of Potassium Chloride in Dextrose and Sodium Chloride Injection did not include sufficient numbers of subjects aged 65 and over to determine whether they respond differently from younger subjects.

Elderly patients are at increased risk of developing hyponatremia as well as for developing hyponatremic encephalopathy [see Warnings and Precautions (5.4)]. Potassium Chloride in Dextrose and Sodium Chloride Injection is known to be substantially excreted by the kidney, and the risk of adverse reactions to this product may be greater in patients with impaired renal function [see Warnings and Precautions (5.2)].

Dose selection for an elderly patient should be cautious, starting at the low end of the dosing range, reflecting the greater frequency of decreased hepatic, renal, or cardiac function, and of concomitant disease or other drug therapy.

8.6 Renal Impairment

Administration of Potassium Chloride in Dextrose and Sodium Chloride Injection in patients with renal impairment may result in hyponatremia, hyperkalemia and/or fluid overload. Monitor patients with renal impairment for development of these adverse reactions [see Warnings and Precautions (5.2, 5.5, 5.6)].

10 OVERDOSAGE

An increased infusion rate of Potassium Chloride in Dextrose and Sodium Chloride Injection can cause:

Hyperkalemia

- Manifestations of hyperkalemia may include:
  - disturbances in cardiac conduction and arrhythmias, including bradycardia, heart block, asystole, ventricular tachycardia, ventricular fibrillation,
  - hypotension,
  - muscle weakness up to and including muscular and respiratory paralysis, paresthesia of extremities,
  - gastrointestinal symptoms (ileus, nausea, vomiting, abdominal pain)
The presence of any ECG findings that are suspected to be caused by hyperkalemia should be considered a medical emergency.
If hyperkalemia is present or suspected, discontinue the infusion immediately and institute close ECG, laboratory and other monitoring and, as necessary, corrective therapy to reduce serum potassium concentrations [see Warnings and Precautions (5.2)].

Other Electrolyte and Fluid Disorders

- hyponatremia, manifestations may include seizures, coma, cerebral edema and death).
- hypernatremia, especially in patients with severe renal impairment.
- fluid overload (which can lead to central and/or peripheral edema).
- Hyperglycemia, hyperosmolality, and adverse effects on water and electrolyte balance, and corresponding complications, which can be fatal [see Warnings and Precautions (5.3, 5.6)].
  Interventions include discontinuation of the infusion, dose reduction, monitoring of fluid balance, electrolyte concentrations and acid-base balance and institution of appropriate corrective measures such as administration of exogenous insulin.

11 DESCRIPTION

Potassium Chloride in Dextrose and Sodium Chloride Injection, USP is a sterile, nonpyrogenic solution for fluid and electrolyte replenishment and caloric supply in a single dose container for intravenous administration. It contains no antimicrobial agents. Composition, osmolarity, pH, ionic concentration and caloric content are shown in Table 1.

Table 1
Table 1 | mEq Potassium/container size | Size (mL) | Composition (g/L) |  |  |  | pH | Ionic Concentration (mEq/L)
Table 1 | mEq Potassium/container size | Size (mL) | ** Dextrose Hydrous, USP | Sodium Chloride, USP (NaCl) | Potassium Chloride, USP (KCl) | [Normal physiologic osmolarity range is approximately 280 to 310 mOsmol/L.] Osmolarity (mOsmol/L) (calc.) | pH | Sodium | Potassium | Chloride | Caloric Content (kCal/L)
Potassium Chloride in 5% Dextrose and 0.2% Sodium Chloride Injection, USP | 20 mEq/L | 1000 | 50 | 2 | 1.5 | 361 | 4.5 (3.5 to 6.5) | 34 | 20 | 54 | 170
Potassium Chloride in 5% Dextrose and 0.2% Sodium Chloride Injection, USP | 10 mEq/500 mL | 500 | 50 | 2 | 1.5 | 361 | 4.5 (3.5 to 6.5) | 34 | 20 | 54 | 170
Potassium Chloride in 5% Dextrose and 0.33% Sodium Chloride Injection, USP | 10 mEq/500 mL | 500 | 50 | 3.3 | 1.5 | 405 | 4.5 (3.5 to 6.5) | 56 | 20 | 76 | 170
Potassium Chloride in 5% Dextrose and 0.45% Sodium Chloride Injection, USP | 10 mEq/L | 1000 | 50 | 4.5 | 0.75 | 426 | 4.5 (3.5 to 6.5) | 77 | 10 | 87 | 170
Potassium Chloride in 5% Dextrose and 0.45% Sodium Chloride Injection, USP | 20 mEq/L | 1000 | 50 | 4.5 | 1.5 | 447 | 4.5 (3.5 to 6.5) | 77 | 20 | 97 | 170
Potassium Chloride in 5% Dextrose and 0.45% Sodium Chloride Injection, USP | 10 mEq/500 mL | 500 | 50 | 4.5 | 1.5 | 447 | 4.5 (3.5 to 6.5) | 77 | 20 | 97 | 170
Potassium Chloride in 5% Dextrose and 0.45% Sodium Chloride Injection, USP | 30 mEq/L | 1000 | 50 | 4.5 | 2.24 | 466 | 4.5 (3.5 to 6.5) | 77 | 30 | 107 | 170
Potassium Chloride in 5% Dextrose and 0.45% Sodium Chloride Injection, USP | 40 mEq/L | 1000 | 50 | 4.5 | 3 | 487 | 4.5 (3.5 to 6.5) | 77 | 40 | 117 | 170
Potassium Chloride in 5% Dextrose and 0.9% Sodium Chloride Injection, USP | 20 mEq/L | 1000 | 50 | 9 | 1.5 | 601 | 4.5 (3.5 to 6.5) | 154 | 20 | 174 | 170
0.9% Sodium Chloride Injection, USP | 40 mEq/L | 1000 | 50 | 9 | 3 | 641 | 4.5 (3.5 to 6.5) | 154 | 40 | 194 | 170

Dextrose is derived from corn.

The VIAFLEX Plus plastic container is fabricated from a specially formulated polyvinyl chloride (PL 146 Plastic). VIAFLEX Plus on the container indicates the presence of a drug additive in a drug vehicle. The VIAFLEX Plus plastic container system utilizes the same container as the VIAFLEX plastic container system. The amount of water that can permeate from inside the container into the overwrap is insufficient to affect the solution significantly. Solutions in contact with the plastic container can leach out certain of its chemical components in very small amounts within the expiration period, e.g., di-2-ethylhexyl phthalate (DEHP), up to 5 parts per million. However, the safety of the plastic has been confirmed in tests in animals according to USP biological tests for plastic containers as well as by tissue culture toxicity studies.

12 CLINICAL PHARMACOLOGY

12.1 Mechanism of Action

Potassium Chloride in Dextrose and Sodium Chloride Injection is a source of water, electrolytes and calories. It is capable of inducing diuresis depending on the clinical condition of the patient.

16 HOW SUPPLIED/STORAGE AND HANDLING

Potassium Chloride in Dextrose and Sodium Chloride Injection, are clear solutions in 500 mL and 1000 mL single-dose, flexible containers available as follows:

Code | Size (mL) | NDC | mEq Potassium | Product Name
2B1614 2B1613 | 1000 500 | 0338-0663-04 0338-0663-03 | 20 mEq/L 10 mEq/L | Potassium Chloride in 5% Dextrose and 0.2% Sodium Chloride Injection, USP
2B1473 | 500 | 0338-0603-03 | 10 mEq/L | Potassium Chloride in 5% Dextrose and 0.33% Sodium Chloride Injection, USP
2B1644 | 1000 | 0338-0669-04 | 10 mEq/L
2B1654 2B1653 2B1664 | 1000 500 1000 | 0338-0671-04 0338-0671-03 0338-0673-04 | 20 mEq/L 10 mEq/L 30 mEq/L | Potassium Chloride in 5% Dextrose and 0.45% Sodium Chloride Injection, USP
2B1674 | 1000 | 0338-0675-04 | 40 mEq/L
2B2434 | 1000 | 0338-0803-04 | 20 mEq/L | Potassium Chloride in 5% Dextrose and
2B2454 | 1000 | 0338-0807-04 | 40 mEq | 0.9% Sodium Chloride Injection, USP

Storage: Avoid excessive heat. Store at room temperature (25°C); brief exposure up to 40°C does not adversely affect the product.

17 PATIENT COUNSELING INFORMATION

Inform patients, caregivers or home healthcare providers of the following risks of Potassium Chloride in Dextrose and Sodium Chloride Injection:

- Hypersensitivity Reactions [see Warnings and Precautions (5.1)]
- Hyperkalemia [see Warnings and Precautions (5.2)]
- Hyperglycemia and hyperosmolar hyperglycemic state [see Warnings and Precautions (5.3)]
- Hyponatremia [see Warnings and Precautions (5.4)]
- Hypernatremia and hyperchloremia [see Warnings and Precautions (5.5)]
- Fluid overload [see Warnings and Precautions (5.6)]
- Refeeding syndrome [see Warnings and Precautions (5.7)]

Baxter Healthcare Corporation
Deerfield, IL 60015 USA
Printed in USA

Distributed in Canada by
Baxter Corporation
Mississauga, ON L5N 0C2

07-19-75-361

Baxter and Viaflex are trademarks of Baxter International Inc.

PACKAGE/LABEL PRINCIPAL DISPLAY PANEL

Container Label

Container Label

2B1614
NDC 0338-0663-04
DIN 00503142

20 mEq

Potassium
Chloride

(20 mEq/L)
Potassium Chloride in 5% Dextrose and
0.2% Sodium Chloride Injection USP

1000 mL
EACH 100 mL CONTAINS 5 g DEXTROSE HYDROUS USP
200 mg SODIUM CHLORIDE USP 150 mg POTASSIUM
CHLORIDE USP pH 4.5 (3.5 TO 6.5) mEq/L SODIUM 34
POTASSIUM 20 CHLORIDE 54 OSMOLARITY 361 mOsmol/L
(CALC) STERILE NONPYROGENIC SINGLE DOSE CONTAINER
ADDITIVES MAY BE INCOMPATIBLE CONSULT WITH PHARMACIST
IF AVAILABLE WHEN INTRODUCING ADDITIVES USE ASEPTIC
TECHNIQUE MIX THOROUGHLY DO NOT STORE DOSAGE
INTRAVENOUSLY AS DIRECTED BY A PHYSICIAN SEE
DIRECTIONS CAUTIONS SQUEEZE AND INSPECT INNER BAG
WHICH MAINTAINS PRODUCT STERILITY DISCARD IF LEAKS ARE
FOUND MUST NOT BE USED IN SERIES CONNECTIONS DO NOT
ADMINISTER SIMULTANEOUSLY WITH BLOOD DO NOT USE
UNLESS SOLUTION IS CLEAR Rx ONLY STORE UNIT IN
MOISTURE BARRIER OVERWRAP AT ROOM TEMPERATURE
(25°C/77°F) UNTIL READY TO USE AVOID EXCESSIVE HEAT
SEE INSERT

VIAFLEX PLUS CONTAINER

PL 146 PLASTIC

BAXTER VIAFLEX AND PL 146 ARE TRADEMARKS OF
BAXTER INTERNATIONAL INC

FOR PRODUCT INFORMATION
1-800-933-0303

Baxter logo
BAXTER HEALTHCARE CORPORATION
DEERFIELD IL 60015 USA

MADE IN USA

1

2

3

4

5

6

7

8

9

Container Label

LOT

EXP

2B1473
NDC 0338-0603-03
DIN 00786241

10 mEq

Potassium
Chloride

(20 mEq/L)
Potassium Chloride in 5% Dextrose and
0.33% Sodium Chloride Injection USP

500 mL
EACH 100 mL CONTAINS 5 g DEXTROSE HYDROUS USP
330 mg SODIUM CHLORIDE USP 150 mg POTASSIUM
CHLORIDE USP pH 4.5 (3.5 TO 6.5) mEq/L
SODIUM 56 POTASSIUM 20 CHLORIDE 76
HYPERTONIC OSMOLARITY 405 mOsmol/L (CALC)
STERILE NONPYROGENIC SINGLE DOSE CONTAINER
ADDITIVES MAY BE INCOMPATIBLE CONSULT WITH
PHARMACIST IF AVAILABLE WHEN INTRODUCING
ADDITIVES USE ASEPTIC TECHNIQUE MIX THOROUGHLY
DO NOT STORE DOSAGE INTRAVENOUSLY AS DIRECTED
BY A PHYSICIAN SEE DIRECTIONS CAUTIONS SQUEEZE
AND INSPECT INNER BAG WHICH MAINTAINS PRODUCT
STERILITY DISCARD IF LEAKS ARE FOUND MUST NOT
BE USED IN SERIES CONNECTIONS DO NOT USE UNLESS SOLUTION IS
CLEAR Rx ONLY STORE UNIT IN MOISTURE BARRIER OVERWRAP AT ROOM TEMPERATURE (25°C/77°F) UNTIL READY TO USE AVOID EXCESSIVE
HEAT SEE INSERT

VIAFLEX PLUS CONTAINER

PL 146 PLASTIC

BAXTER VIAFLEX AND PL 146 ARE TRADEMARKS OF
BAXTER INTERNATIONAL INC

FOR PRODUCT INFORMATION
1-800-933-0303

Baxter logo
BAXTER HEALTHCARE CORPORATION
DEERFIELD IL 60015 USA

MADE IN USA

Container Label

Container Label

LOT

EXP

2B1644
NDC 0338-0669-04
DIN 00790109

10 mEq

Potassium
Chloride

(10 mEq/L)
Potassium Chloride in 5% Dextrose and
0.45% Sodium Chloride Injection USP

1000 mL
EACH 100 mL CONTAINS 5 g DEXTROSE HYDROUS USP
450 mg SODIUM CHLORIDE USP 75 mg POTASSIUM
CHLORIDE USP pH 4.5 (3.5 TO 6.5) mEq/L
SODIUM 77 POTASSIUM 10 CHLORIDE 87
HYPERTONIC OSMOLARITY 426 mOsmol/L (CALC)
STERILE NONPYROGENIC SINGLE DOSE CONTAINER
ADDITIVES MAY BE INCOMPATIBLE CONSULT WITH
PHARMACIST IF AVAILABLE WHEN INTRODUCING
ADDITIVES USE ASEPTIC TECHNIQUE MIX THOROUGHLY
DO NOT STORE DOSAGE INTRAVENOUSLY AS DIRECTED
BY A PHYSICIAN SEE DIRECTIONS CAUTIONS SQUEEZE
AND INSPECT INNER BAG WHICH MAINTAINS PRODUCT
STERILITY DISCARD IF LEAKS ARE FOUND MUST NOT
BE USED IN SERIES CONNECTIONS DO NOT USE UNLESS
SOLUTION IS CLEAR Rx ONLY STORE UNIT IN
MOISTURE BARRIER OVERWRAP AT ROOM TEMPERATURE
(25°C/77°F) UNTIL READY TO USE AVOID EXCESSIVE HEAT
SEE INSERT

VIAFLEX PLUS CONTAINER

PL 146 PLASTIC

BAXTER VIAFLEX AND PL 146 ARE TRADEMARKS OF
BAXTER INTERNATIONAL INC

FOR PRODUCT INFORMATION 1-800-933-0303

Baxter logo
BAXTER HEALTHCARE CORPORATION
DEERFIELD IL 60015 USA

MADE IN USA

1
2
3
4
5
6
7
8
9

Container Label

Container Label

2B1653
NDC 0338-0671-03
DIN 00437999

10 mEq

Potassium
Chloride

(20 mEq/L)
Potassium Chloride in 5% Dextrose and
0.45% Sodium Chloride Injection USP

500 mL
EACH 100 mL CONTAINS 5 g DEXTROSE HYDROUS USP 450 mg SODIUM
CHLORIDE USP 150 mg POTASSIUM CHLORIDE USP pH 4.5 (3.5 TO
6.5) mEq/L SODIUM 77 POTASSIUM 20 CHLORIDE 97 HYPERTONIC
OSMOLARITY 447 mOsmol/L (CALC) STERILE NONPYROGENIC SINGLE
DOSE CONTAINER ADDITIVES MAY BE INCOMPATIBLE CONSULT WITH
PHARMACIST IF AVAILABLE WHEN INTRODUCING ADDITIVES USE ASEPTIC TECHNIQUE MIX THOROUGHLY DO NOT STORE DOSAGE INTRAVENOUSLY
AS DIRECTED BY A PHYSICIAN SEE DIRECTIONS CAUTIONS SQUEEZE AND INSPECT INNER BAG WHICH MAINTAINS PRODUCT STERILITY DISCARD IF
LEAKS ARE FOUND MUST NOT BE USED IN SERIES CONNECTIONS DO NOT
USE UNLESS SOLUTION IS CLEAR Rx ONLY STORE UNIT IN MOISTURE
BARRIER OVERWRAP AT ROOM TEMPERATURE (25°C/77°F) UNTIL READY TO
USE AVOID EXCESSIVE HEAT SEE INSERT

Baxter logo
BAXTER HEALTHCARE CORPORATION
DEERFIELD IL 60015 USA

MADE IN USA

DISTRIBUTED IN CANADA BY
BAXTER CORPORATION
MISSISSAUGA ON L5N 0C2

VIAFLEX PLUS CONTAINER
PL 146 PLASTIC

FOR PRODUCT INFORMATION
1-800-933-0303

BAXTER VIAFLEX AND PL 146 ARE TRADEMARKS OF
BAXTER INTERNATIONAL INC

1

2

3

4

Container Label

Container Label

LOT

EXP

2B1664
NDC 0338-0673-04
DIN 00786284

30 mEq

Potassium
Chloride

(30 mEq/L)
Potassium Chloride in 5% Dextrose and
0.45% Sodium Chloride Injection USP

1000 mL
EACH 100 mL CONTAINS 5 g DEXTROSE HYDROUS USP
450 mg SODIUM CHLORIDE USP 224 mg POTASSIUM
CHLORIDE USP pH 4.5 (3.5 TO 6.5) mEq/L
SODIUM 77 POTASSIUM 30 CHLORIDE 107
HYPERTONIC OSMOLARITY 466 mOsmol/L (CALC)
STERILE NONPYROGENIC SINGLE DOSE CONTAINER
ADDITIVES MAY BE INCOMPATIBLE CONSULT WITH
PHARMACIST IF AVAILABLE WHEN INTRODUCING
ADDITIVES USE ASEPTIC TECHNIQUE MIX THOROUGHLY
DO NOT STORE DOSAGE INTRAVENOUSLY AS DIRECTED
BY A PHYSICIAN SEE DIRECTIONS CAUTIONS SQUEEZE
AND INSPECT INNER BAG WHICH MAINTAINS PRODUCT
STERILITY DISCARD IF LEAKS ARE FOUND MUST NOT
BE USED IN SERIES CONNECTIONS DO NOT USE UNLESS
SOLUTION IS CLEAR Rx ONLY STORE UNIT IN
MOISTURE BARRIER OVERWRAP AT ROOM TEMPERATURE
(25°C/77°F) UNTIL READY TO USE AVOID EXCESSIVE HEAT
SEE INSERT

VIAFLEX PLUS CONTAINER
PL 146 PLASTIC

BAXTER VIAFLEX AND PL 146 ARE TRADEMARKS OF
BAXTER INTERNATIONAL INC

FOR PRODUCT INFORMATION
1-800-933-0303

Baxter logo
BAXTER HEALTHCARE CORPORATION
DEERFIELD IL 60015 USA

MADE IN USA

1
2
3
4
5
6
7
8
9

Container Label

Container Label

LOT

EXP

2B1674
NDC 0338-0675-04
DIN 00438006

40 mEq

Potassium
Chloride

(40 mEq/L)
Potassium Chloride in 5% Dextrose and
0.45% Sodium Chloride Injection USP

1000 mL
EACH 100 mL CONTAINS 5 g DEXTROSE HYDROUS USP
450 mg SODIUM CHLORIDE USP 300 mg POTASSIUM
CHLORIDE USP pH 4.5 (3.5 TO 6.5) mEq/L
SODIUM 77 POTASSIUM 40 CHLORIDE 117
HYPERTONIC OSMOLARITY 487 mOsmol/L (CALC)
STERILE NONPYROGENIC SINGLE DOSE CONTAINER
ADDITIVES MAY BE INCOMPATIBLE CONSULT WITH
PHARMACIST IF AVAILABLE WHEN INTRODUCING
ADDITIVES USE ASEPTIC TECHNIQUE MIX THOROUGHLY
DO NOT STORE DOSAGE INTRAVENOUSLY AS DIRECTED
BY A PHYSICIAN SEE DIRECTIONS CAUTIONS SQUEEZE
AND INSPECT INNER BAG WHICH MAINTAINS PRODUCT
STERILITY DISCARD IF LEAKS ARE FOUND MUST NOT
BE USED IN SERIES CONNECTIONS DO NOT USE UNLESS
SOLUTION IS CLEAR Rx ONLY STORE UNIT IN
MOISTURE BARRIER OVERWRAP AT ROOM TEMPERATURE
(25°C/77°F) UNTIL READY TO USE AVOID EXCESSIVE HEAT
SEE INSERT

VIAFLEX PLUS CONTAINER
PL 146 PLASTIC

BAXTER VIAFLEX AND PL 146 ARE TRADEMARKS OF
BAXTER INTERNATIONAL INC

FOR PRODUCT INFORMATION
1-800-933-0303

Baxter logo
BAXTER HEALTHCARE CORPORATION
DEERFIELD IL 60015 USA

MADE IN USA

1
2
3
4
5
6
7
8
9

Container Label

Container Label

LOT

EXP

2B2434
NDC 0338-0803-04
DIN 00786292

20 mEq
Potassium
Chloride

(20 mEq/L)
Potassium Chloride in 5% Dextrose and
0.9% Sodium Chloride Injection USP

1000 mL
EACH 100 mL CONTAINS 5 g DEXTROSE HYDROUS USP
900 mg SODIUM CHLORIDE USP 150 mg POTASSIUM
CHLORIDE USP pH 4.5 (3.5 TO 6.5) mEq/L
SODIUM 154 POTASSIUM 20 CHLORIDE 174
OSMOLARITY 601 mOsmol/L (CALC) HYPERTONIC
MAY CAUSE VEIN DAMAGE STERILE NONPYROGENIC
SINGLE DOSE CONTAINER ADDITIVES MAY BE INCOMPATIBLE
CONSULT WITH PHARMACIST IF AVAILABLE WHEN INTRODUCING
ADDITIVES USE ASEPTIC TECHNIQUE MIX THOROUGHLY
DO NOT STORE DOSAGE INTRAVENOUSLY AS DIRECTED
BY A PHYSICIAN SEE DIRECTIONS CAUTIONS SQUEEZE
AND INSPECT INNER BAG WHICH MAINTAINS PRODUCT
STERILITY DISCARD IF LEAKS ARE FOUND MUST NOT
BE USED IN SERIES CONNECTIONS DO NOT USE UNLESS
SOLUTION IS CLEAR Rx ONLY STORE UNIT IN
MOISTURE BARRIER OVERWRAP AT ROOM TEMPERATURE
(25°C/77°F) UNTIL READY TO USE AVOID EXCESSIVE HEAT
SEE INSERT

VIAFLEX PLUS CONTAINER
PL 146 PLASTIC

BAXTER VIAFLEX AND PL 146 ARE TRADEMARKS OF
BAXTER INTERNATIONAL INC

FOR PRODUCT INFORMATION
1-800-933-0303

Baxter logo
BAXTER HEALTHCARE CORPORATION
DEERFIELD IL 60015 USA

MADE IN USA

1
2
3
4
5
6
7
8
9

Container Label

Container Label

LOT EXP

2B2454
NDC 0338-0807-04
DIN 00786306

40 mEq
Potassium
Chloride

(40 mEq/L)
Potassium Chloride in 5% Dextrose and
0.9% Sodium Chloride Injection USP

1000 mL
EACH 100 mL CONTAINS 5 g DEXTROSE HYDROUS USP 900
mg SODIUM CHLORIDE USP 300 mg POTASSIUM CHLORIDE
USP pH 4.5 (3.5 TO 6.5) mEq/L SODIUM 154
POTASSIUM 40 CHLORIDE 194 OSMOLARITY 641
mOsmol/L (CALC) HYPERTONIC MAY CAUSE VEIN DAMAGE
STERILE NONPYROGENIC SINGLE DOSE CONTAINER
ADDITIVES MAY BE INCOMPATIBLE CONSULT WITH PHARMACIST
IF AVAILABLE WHEN INTRODUCING ADDITIVES USE ASEPTIC
TECHNIQUE MIX THOROUGHLY DO NOT STORE DOSAGE
INTRAVENOUSLY AS DIRECTED BY A PHYSICIAN SEE DIRECTIONS
CAUTIONS SQUEEZE AND INSPECT INNER BAG WHICH MAINTAINS
PRODUCT STERILITY DISCARD IF LEAKS ARE FOUND MUST NOT
BE USED IN SERIES CONNECTIONS DO NOT USE UNLESS
SOLUTION IS CLEAR Rx ONLY STORE UNIT IN MOISTURE
BARRIER OVERWRAP AT ROOM TEMPERATURE (25°C/77°F)
UNTIL READY TO USE AVOID EXCESSIVE HEAT SEE INSERT

VIAFLEX PLUS CONTAINER PL 146 PLASTIC

BAXTER VIAFLEX AND PL 146 ARE TRADEMARKS OF
BAXTER INTERNATIONAL INC

FOR PRODUCT INFORMATION 1-800-933-0303

Baxter logo
BAXTER HEALTHCARE CORPORATION
DEERFIELD IL 60015 USA

MADE IN USA

DISTRIBUTED IN CANADA BY
BAXTER CORPORATION
MISSISSAUGA ON L5N 0C2

1

2

3

5

6

7

8

9